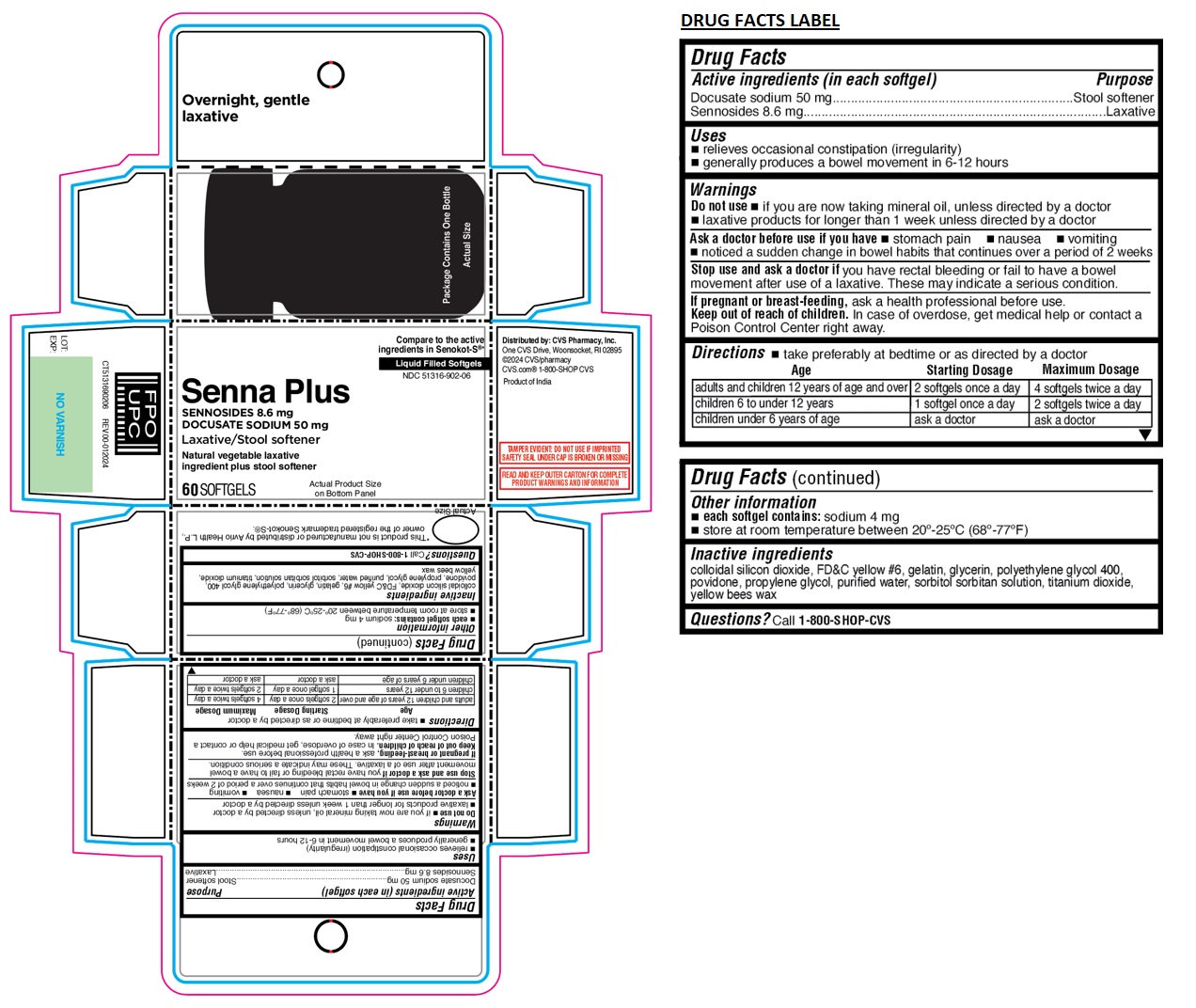 DRUG LABEL: CVS Health Senna Plus Stool Softener Laxative Softgel
NDC: 51316-902 | Form: CAPSULE, LIQUID FILLED
Manufacturer: CVS Pharmacy, Inc.
Category: otc | Type: HUMAN OTC DRUG LABEL
Date: 20240117

ACTIVE INGREDIENTS: DOCUSATE SODIUM 50 mg/1 1; SENNOSIDES 8.6 mg/1 1
INACTIVE INGREDIENTS: SILICON DIOXIDE; FD&C YELLOW NO. 6; GELATIN, UNSPECIFIED; GLYCERIN; POLYETHYLENE GLYCOL 400; POVIDONE, UNSPECIFIED; PROPYLENE GLYCOL; WATER; SORBITOL; SORBITAN; TITANIUM DIOXIDE; YELLOW WAX

CVS Health Senna Plus Laxative/Stool softener Softgels

Active ingredients (in each softgel)

Docusate sodium 50 mg
Sennosides 8.6 mg

Purpose

Stool softener
Laxative

Uses

• relieves occasional constipation (irregularity)
• generally produces a bowel movement in 6-12 hours

Warnings

Do not use • if you are now taking mineral oil, unless directed by a doctor • laxative products for longer than 1 week unless directed by a doctor

Ask a doctor before use if you have • stomach pain • nausea • vomiting • noticed a sudden change in bowel habits that continues over a period of 2 weeks

Stop use and ask a doctor if you have rectal bleeding or fail to have a bowel movement after use of a laxative. These may indicate a serious condition.

If pregnant or breast-feeding, ask a health professional before use.

Keep out of reach of children. In case of overdose, get medical help or contact a Poison Control Center right away.

Directions

• take preferably at bedtime or as directed by a doctor

Age | Starting Dosage | Maximum Dosage
adults and children 12 years of age and over | 2 softgels once a day | 4 softgels twice a day
children 6 to under 12 years | 1 softgel once a day | 2 softgels twice a day
children under 6 years of age | ask a doctor | ask a doctor

Other information

• each softgel contains: sodium 4 mg
• store at room temperature between 20°-25°C (68°-77°F)

Inactive ingredients

colloidal silicon dioxide, FD&C yellow #6, gelatin, glycerin, polyethylene glycol 400, povidone, propylene glycol, purified water, sorbitol sorbitan solution, titanium dioxide, yellow bees wax

Questions?

Call 1-800-SHOP-CVS

Compare to the active ingredients in Senokot-S®*

Liquid Filled Softgels

Natural vegetable laxative ingredient plus stool softener

Actual Product Size on Bottom Panel

*This product is not manufactured or distributed by Avrio Health L.P., owner of the registered trademark Senokot-S®*.

Package Contains One Bottle

Overnight, gentle laxative

Distributed by: CVS Pharmacy, Inc.
One CVS Drive, Woonsocket, RI 02895
@2024 CVS/pharmacy
CVS.com® 1-800-SHOP CVS

Product of India

TAMPER EVIDENT: DO NOT USE IF IMPRINTED SAFETY SEAL UNDER CAP IS BROKEN OR MISSING

READ AND KEEP OUTER CARTON FOR COMPLETE PRODUCT WARNINGS AND INFORMATION